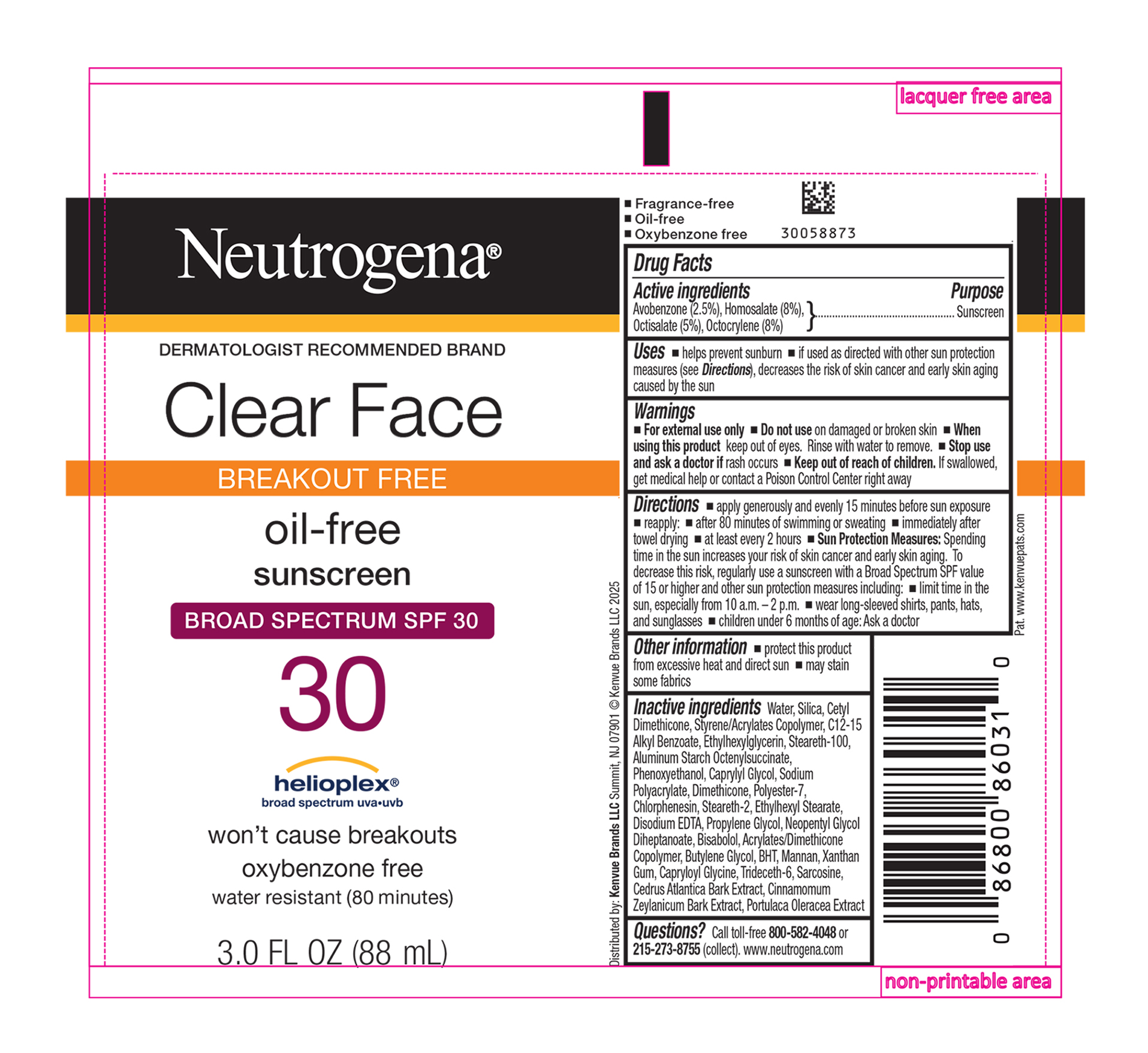 DRUG LABEL: Neutrogena Clear Face Breakout Free Oil Free Sunscreen Broad Spectrum SPF 30
NDC: 69968-0571 | Form: LOTION
Manufacturer: Kenvue Brands LLC
Category: otc | Type: HUMAN OTC DRUG LABEL
Date: 20250821

ACTIVE INGREDIENTS: AVOBENZONE 25 mg/1 mL; HOMOSALATE 80 mg/1 mL; OCTISALATE 50 mg/1 mL; OCTOCRYLENE 80 mg/1 mL
INACTIVE INGREDIENTS: 2-ETHYLHEXYL ACRYLATE, METHACRYLATE, METHYL METHACRYLATE, OR BUTYL METHACRYLATE/HYDROXYPROPYL DIMETHICONE COPOLYMER (30000-300000 MW); SILICON DIOXIDE; ALKYL (C12-15) BENZOATE; ETHYLHEXYLGLYCERIN; STEARETH-100; ALUMINUM STARCH OCTENYLSUCCINATE; PHENOXYETHANOL; CAPRYLYL GLYCOL; DIMETHICONE; POLYESTER-7; CHLORPHENESIN; STEARETH-2; ETHYLHEXYL STEARATE; WATER; EDETATE DISODIUM ANHYDROUS; PROPYLENE GLYCOL; NEOPENTYL GLYCOL DIHEPTANOATE; LEVOMENOL; BUTYL METHACRYLATE/METHYL METHACRYLATE/METHACRYLIC ACID/STYRENE CROSSPOLYMER; BUTYLENE GLYCOL; BUTYLATED HYDROXYTOLUENE; YEAST MANNAN; XANTHAN GUM; CAPRYLOYL GLYCINE; TRIDECETH-6; SARCOSINE; CEDRUS ATLANTICA BARK; CINNAMON BARK OIL; PURSLANE; CETYL DIMETHICONE 25

Neutrogena® Clear Face BREAKOUT FREE oil-free sunscreen BROAD SPECTRUM SPF 30

Drug Facts

ACTIVE INGREDIENT

Active ingredients | Purpose
Avobenzone 2.5% | Sunscreen
Homosalate 8% | Sunscreen
Octisalate 5% | Sunscreen
Octocrylene 8% | Sunscreen

Uses

- helps prevent sunburn
- if used as directed with other sun protection measures (see Directions), decreases the risk of skin cancer and early skin aging caused by the sun

Warnings

- For external use only

- Do not use on damaged or broken skin

- When using this product keep out of eyes. Rinse with water to remove.

- Stop use and ask a doctor if rash occurs

- Keep out of reach of children. If swallowed, get medical help or contact a Poison Control Center right away

Directions

- apply generously and evenly 15 minutes before sun exposure
- reapply:
- after 80 minutes of swimming or sweating
- immediately after towel drying
- at least every 2 hours
- Sun Protection Measures. Spending time in the sun increases your risk of skin cancer and early skin aging. To decrease this risk, regularly use a sunscreen with a Broad Spectrum SPF value of 15 or higher and other sun protection measures including:
- limit time in the sun, especially from 10 a.m. – 2 p.m.
- wear long-sleeved shirts, pants, hats, and sunglasses
- Children under 6 months of age: Ask a doctor

Other information

- protect this product from excessive heat and direct sun
- may stain some fabrics

Inactive ingredients

Water, Silica, Cetyl Dimethicone, Styrene/Acrylates Copolymer, C12-15 Alkyl Benzoate, Ethylhexylglycerin, Steareth-100, Aluminum Starch Octenylsuccinate, Phenoxyethanol, Caprylyl Glycol, Sodium Polyacrylate, Dimethicone, Polyester-7, Chlorphenesin, Steareth-2, Ethylhexyl Stearate, Disodium EDTA, Propylene Glycol, Neopentyl Glycol Diheptanoate, Bisabolol, Acrylates/Dimethicone Copolymer, Butylene Glycol, BHT, Mannan, Xanthan Gum, Capryloyl Glycine, Trideceth-6, Sarcosine, Cedrus Atlantica Bark Extract, Cinnamomum Zeylanicum Bark Extract, Portulaca Oleracea Extract

Questions?

Call toll‐free 800-582-4048 or 215‐273‐8755 (collect). www.neutrogena.com

Distributed by:

Kenvue Brands LLC
Summit, NJ 07901

PRINCIPAL DISPLAY PANEL - 88 mL Tube Label

Neutrogena®
DERMATOLOGIST RECOMMENDED BRAND

Clear Face
BREAKOUT FREE
oil-free
sunscreen
BROAD SPECTRUM SPF 30

30

helioplex®
broad spectrum uva•uvb

won't cause breakouts
oxybenzone free

water resistant (80 minutes)

3.0 FL OZ (88 mL)